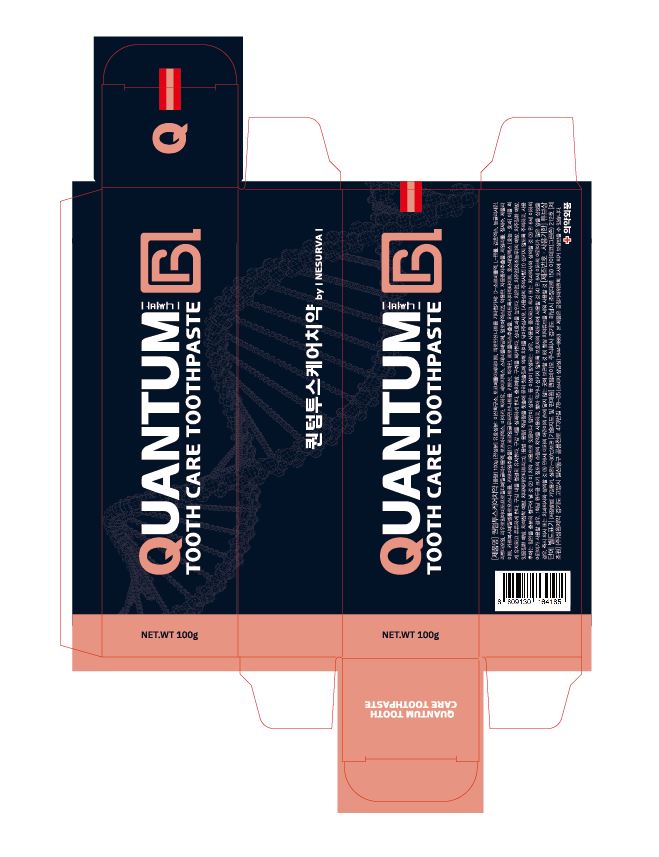 DRUG LABEL: QUANTUMTOOTHCARE TOOTH
NDC: 81659-0001 | Form: PASTE, DENTIFRICE
Manufacturer: HealingStory.,LTD.
Category: otc | Type: HUMAN OTC DRUG LABEL
Date: 20210304

ACTIVE INGREDIENTS: SILICON DIOXIDE 14 g/100 g; .ALPHA.-TOCOPHEROL ACETATE 0.1 g/100 g; SODIUM PYROPHOSPHATE 0.5 g/100 g
INACTIVE INGREDIENTS: XYLITOL; WATER; TRIBASIC CALCIUM PHOSPHATE

ACTIVE INGREDIENT

Silicon Dioxide

Tocopherol Acetate

Tetrasodium Pyrophosphate

INACTIVE INGREDIENT

D-Sorbitol Solution

Concentrated Glycerin
Carboxymethylcellulose Sodium

Hydroxyapatite

Medicinal Carbon

Chitosan

Mica

Zeolite

Xylitol

Steviol Glycoside

Papain

Grapefruit Seed Extract

L-Menthol

Mentha Oil

Propolis Extract

Chamomile Extract

Rosemary Extract

Sage Extract

Aloe Extract

Glycyrrhiza Extract

Horsetail Extract

Lavender Oil

Sodium Cocoyl Glutamate

Lauroyl Amidopropyl Dimethyl Glycine Solution

Deionized Water

PURPOSE

For dental care

Keep out of reach of children

INDICATIONS AND USAGE

Apply an appropriate amount to your toothbrush and brush your teeth by brushing.

Warnings

Keep out of reach of children

■ If more than used for rinsing is accidentally swallowed, get medical help or contact a Poison Control Center right away.

Other Information

■ Store in an airtight container at room temperature

■ Date of use : 36 months from the date of manufacture

DOSAGE AND ADMINISTRATION

For dental use only